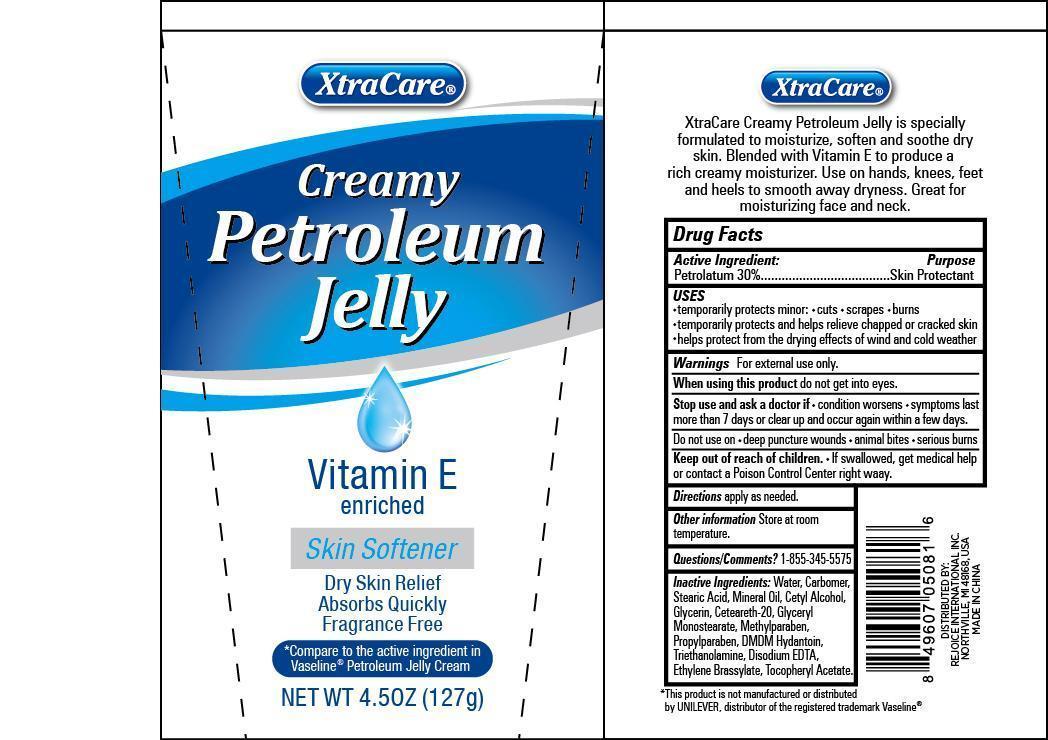 DRUG LABEL: XtraCare Creamy Petroleum Jelly
NDC: 57337-061 | Form: JELLY
Manufacturer: Rejoice International
Category: otc | Type: HUMAN OTC DRUG LABEL
Date: 20250211

ACTIVE INGREDIENTS: PETROLATUM 38 g/127 g
INACTIVE INGREDIENTS: CARBOMER COPOLYMER TYPE A (ALLYL PENTAERYTHRITOL CROSSLINKED); STEARIC ACID; MINERAL OIL; CETYL ALCOHOL; GLYCERIN; POLYOXYL 20 CETOSTEARYL ETHER; GLYCERYL MONOSTEARATE; WATER; METHYLPARABEN; PROPYLPARABEN; DMDM HYDANTOIN; TROLAMINE; EDETATE DISODIUM; ETHYLENE BRASSYLATE; TOCOPHEROL

XtraCare Creamy Petroleum Jelly

Active Ingredient: Purpose

Petrolatum 30% ........................... Skin Protectant

Uses

- temporarily protects minor cuts, scrapes, burns
- temporarily protects and helps relieve chapped or cracked skin
- helps protect from the drying effects of wind and cold weather

Keep out of reach of children. If swallowed, get medical help or contact a Poison Control Center right away.

INDICATIONS AND USAGE

XtraCare® Creamy Petroleum Jelly

Vitamin E Enriched

Skin Softener

Dry Skin Relief

Absorbs Quickly

Fragrance Free

*Compare to the active ingredient in Vaseline® Petroleum Jelly Cream

Net Wt 4.5oz (127g)

XtraCare®

XtraCare Creamy Petroleum Jelly is specially formulated to moisturize, soften and soothe dry skin. Blended with Vitamin E to produce a rich creamy moisturizer. Use on hands, knees, feet and heels to smooth away dryness. Great for moisturizing face and neck.

Warnings

for external use only.

When using this product do not get into eyes.

Stop use and ask a doctor if

- condition worsens
- symptoms last more than 7 days or clear up and occur again within a few days.

Do not use on

- deep puncture wounds
- animal bites
- serious burns

DOSAGE AND ADMINISTRATION

Directions apply as needed.

Inactive Ingredients

water, carbomer, stearic acid, mineral oil, cetyl alcohol, glycerin, ceteareth-20, glyceryl monostearate, methylparaben, propylparaben, DMDM hydantoin, triethanolamine, disodium EDTA, ethylene brassylate, tocopheryl acetate.

Other Information store at room temperature.

Questions/Comments? 1-855-345-5575

*this product is not manufactured or distributed by UNILEVER, distributor of the registered trademark Vaseline®

DISTRIBUTED BY

REJOICE INTERNATIONAL INC

NORTHVILLE, MI 48168 USA

MADE IN CHINA